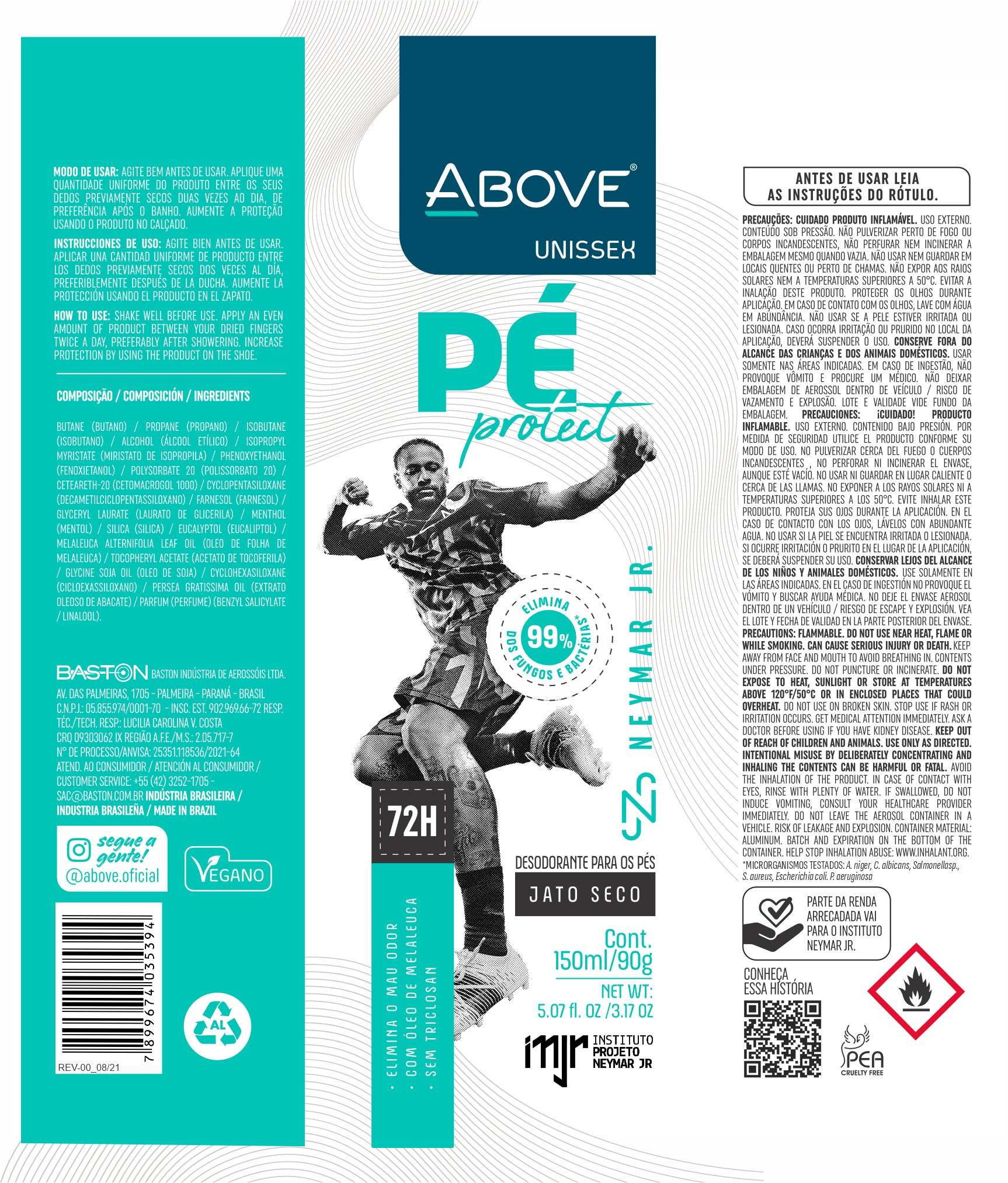 DRUG LABEL: Above foot Protect Neymar Jr Unissex
NDC: 73306-1153 | Form: AEROSOL, SPRAY
Manufacturer: BASTON INDUSTRIA DE AEROSSOIS LTDA
Category: otc | Type: HUMAN OTC DRUG LABEL
Date: 20241226

ACTIVE INGREDIENTS: FARNESOL 3 mg/100 g
INACTIVE INGREDIENTS: ISOBUTANE

Above foot Protect Neymar Jr Unissex

ACTIVE INGREDIENT

FARNESOL

PURPOSE

FOOT DEODORANT

INDICATIONS AND USAGE

SHAKE WELL BEFORE USE. APPLY NA EVEN AMOUNT OF PRODUCT BETWEEN YOUR DRIED FINGERS TWICE A DAY, PREFERABLY AFTER SHOWERING. INCREASE PROTECTION BY USING THE PRODUCT ON THE SHOE

INACTIVE INGREDIENT

BUTANE(BUTANO)/PROPANE(PROPANO)/ISOBUTANE(ISOBUTANO)/ALCOHOL(ÁLCOOL ETÍLICO)/ISOPROPYL MYRISTATE(MIRISTATO DE ISOPROPILA)/PHENOXYETHANOL(FENOXIETANOL)/POLYSORBATE 20(POLISSORBATO 20)/CETEARETH-20(CETOMACROGOL 1000) / CYCLOPENTASILOXANE(DECAMETILCICLOPENTASSILOXANO)GLYCERYL LAURATE(LAURATO DE GLICERILA)/MENTHOL(MENTOL)/SILICA(SILICA)/EUCALYPTOL(EUCALIPTOL)/MELALEUCA ALTERNIFOLIA LEAF OIL(OLEO DE FOLHA DE MELALEUCA)/TOCOPHERYL ACETATE(ACETATO DE TOCOFERILA)/GLYCINE SOJA OIL(OLEO DE SOJA)/CYCLOHEXASILOXANE(CICLOEXASSILOXANO)/PERSEA GRATISSIMA OIL (EXTRATO OLEOSO DE ABACATE)/

WARNINGS AND PRECAUTIONS

FLAMMABLE. DO NOT USE NEAR HEAT, FLAME OR WHILE SMOKING. CAN CAUSE SERIOUS INJURY OR DEATH KEEP AWAY FROM FACE AND MOUTH TO AVOID BREATHING IN AVOID SPRAYING IN EYES. CONTENTS UNDER PRESSURE. DO NOT PUNCTURE OR INCINERATE. DO NOT EXPOSE TO HEAT, SUNLIGHT OR STORE AT TEMPERATURES ABOVE 120°F/50°C OR IN ENCLOSED PLACES THAT COULD OVERHEAT DO NOT USE ON BROKEN SKIN. STOP USE IF RASH OR IRRITATION OCCURS. GET MEDICAL ATTENTION IMMEDIATELY ASK A DOCTOR BEFORE USING IF YOU HAVE KIDNEY DISEASE KEEP OUT OF REACH OF CHILDREN AND ANIMALS USE ONLY AS DIRECTED. INTENTIONAL MISUSE BY DELIBERATELY CONCENTRATING AND INHALING THE CONTENTS CAN BE HARMFUL OR FATAL AVOID THE INHALATION OF THE PRODUCT IN CASE OF CONTACT WITH EYES, RINSE WITH PLENTY OF WATER IF SWALLOWED, DO NOT INDUCE VOMITING; CONSULT YOUR HEALTHCARE PROVIDER IMMEDIATELY DO NOT LEAVE THE AEROSOL CONTAINER IN A VEHICLE. RISK OF LEAKAGE AND EXPLOSION. CONTAINER MATERIAL: ALUMINUM BATCH AND EXPIRATION ON THE BOTTOM OF THE CONTAINER. HELP STOP INHALATION ABUSE: WWW.INHALANT.ORG

WARNINGS

FLAMMABLE. DO NOT USE NEAR HEAT, FLAME OR WHILE SMOKING. CAN CAUSE SERIOUS INJURY OR DEATH KEEP AWAY FROM FACE AND MOUTH TO AVOID BREATHING IN AVOID SPRAYING IN EYES. CONTENTS UNDER PRESSURE. DO NOT PUNCTURE OR INCINERATE. DO NOT EXPOSE TO HEAT, SUNLIGHT OR STORE AT TEMPERATURES ABOVE 120°F/50°C OR IN ENCLOSED PLACES THAT COULD OVERHEAT DO NOT USE ON BROKEN SKIN. STOP USE IF RASH OR IRRITATION OCCURS. GET MEDICAL ATTENTION IMMEDIATELY ASK A DOCTOR BEFORE USING IF YOU HAVE KIDNEY DISEASE KEEP OUT OF REACH OF CHILDREN AND ANIMALS USE ONLY AS DIRECTED. INTENTIONAL MISUSE BY DELIBERATELY CONCENTRATING AND INHALING THE CONTENTS CAN BE HARMFUL OR FATAL AVOID THE INHALATION OF THE PRODUCT IN CASE OF CONTACT WITH EYES, RINSE WITH PLENTY OF WATER IF SWALLOWED, DO NOT INDUCE VOMITING; CONSULT YOUR HEALTHCARE PROVIDER IMMEDIATELY DO NOT LEAVE THE AEROSOL CONTAINER IN A VEHICLE. RISK OF LEAKAGE AND EXPLOSION. CONTAINER MATERIAL: ALUMINUM BATCH AND EXPIRATION ON THE BOTTOM OF THE CONTAINER. HELP STOP INHALATION ABUSE: WWW.INHALANT.ORG

DOSAGE AND ADMINISTRATION

make use of it whenever you find it necessary

INDICATIONS AND USAGE

SHAKE WELL BEFORE USE. APPLY NA EVEN AMOUNT OF PRODUCT BETWEEN YOUR DRIED FINGERS TWICE A DAY, PREFERABLY AFTER SHOWERING. INCREASE PROTECTION BY USING THE PRODUCT ON THE SHOE

KEEP OUT OF REACH OF CHILDREN